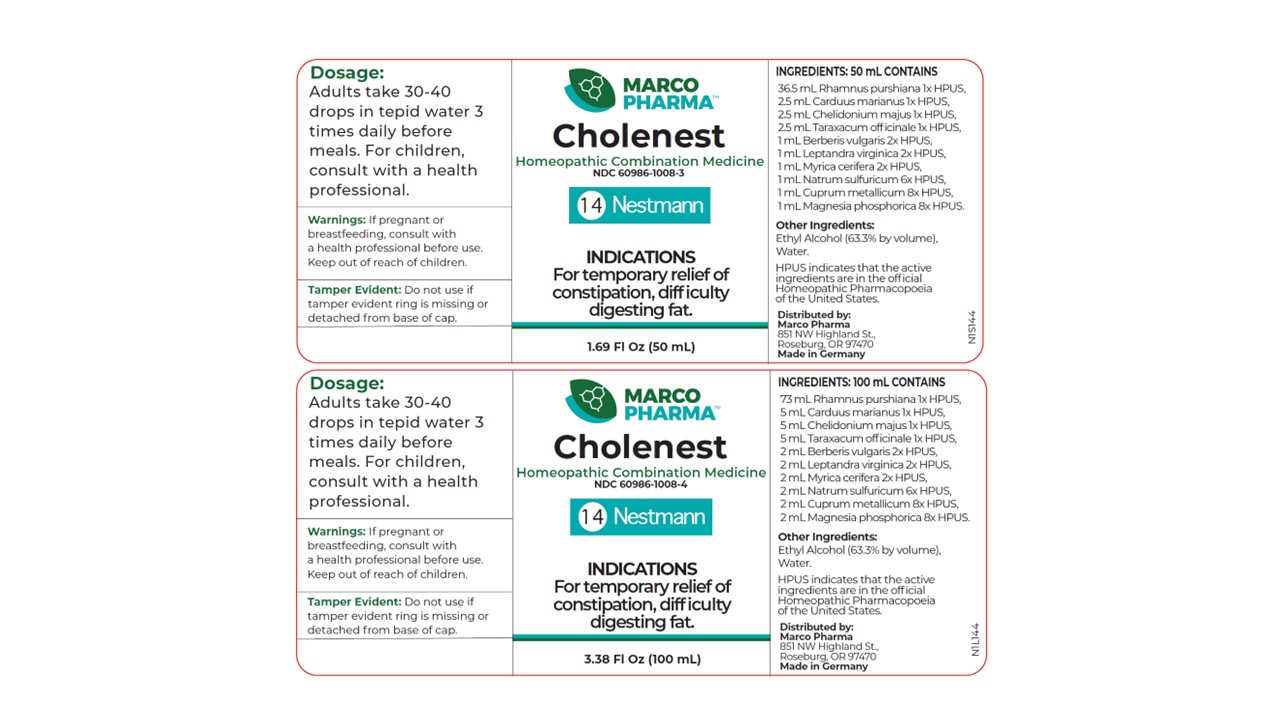 DRUG LABEL: Cholenest
NDC: 60986-1008 | Form: LIQUID
Manufacturer: Marco Pharma International LLC.
Category: homeopathic | Type: HUMAN OTC DRUG LABEL
Date: 20260112

ACTIVE INGREDIENTS: FRANGULA PURSHIANA BARK 1 [hp_X]/100 mL; SILYBUM MARIANUM SEED 1 [hp_X]/100 mL; TARAXACUM OFFICINALE 1 [hp_X]/100 mL; CHELIDONIUM MAJUS 1 [hp_X]/100 mL; VERONICASTRUM VIRGINICUM ROOT 2 [hp_X]/100 mL; MORELLA CERIFERA ROOT BARK 2 [hp_X]/100 mL; BERBERIS VULGARIS ROOT BARK 2 [hp_X]/100 mL; SODIUM SULFATE 6 [hp_X]/100 mL; MAGNESIUM PHOSPHATE, DIBASIC TRIHYDRATE 8 [hp_X]/100 mL; COPPER 8 [hp_X]/100 mL
INACTIVE INGREDIENTS: ALCOHOL; WATER

Drug Facts

Active Ingredients

Cascara sagrada 1xHPUS

Milk thistle 1xHPUS

Dandelion 1xHPUS

Celadine 1xHPUS

Culver's root 2xHPUS

Bayberry 2xHPUS

Barberry 2xHPUS

Disodium sulfate 6xHPUS

Magnesium hydrogen phosphate 8xHPUS

Metallic copper 8XHPUS

The letters HPUS indicates that the components in this product are officially monographed in the Homeopathic Pharmacopoeia of United Sates.

Purpose

Relief of constipation, difficulty digesting fat.

Keep out of reach of children.

Suggested use

Adults: 30-40 drops in tepid water 3 times daily before meals. Children, 10 drops in tepid water 3 times daily before meals.

Warnings

If pregnant or breast-feeding, consult a health professional before use.

DOSAGE AND ADMINISTRATION

(Read Suggested Use Section)

Inactive Ingredients

Ethyl Alcohol (63.3% by vol.) and Water